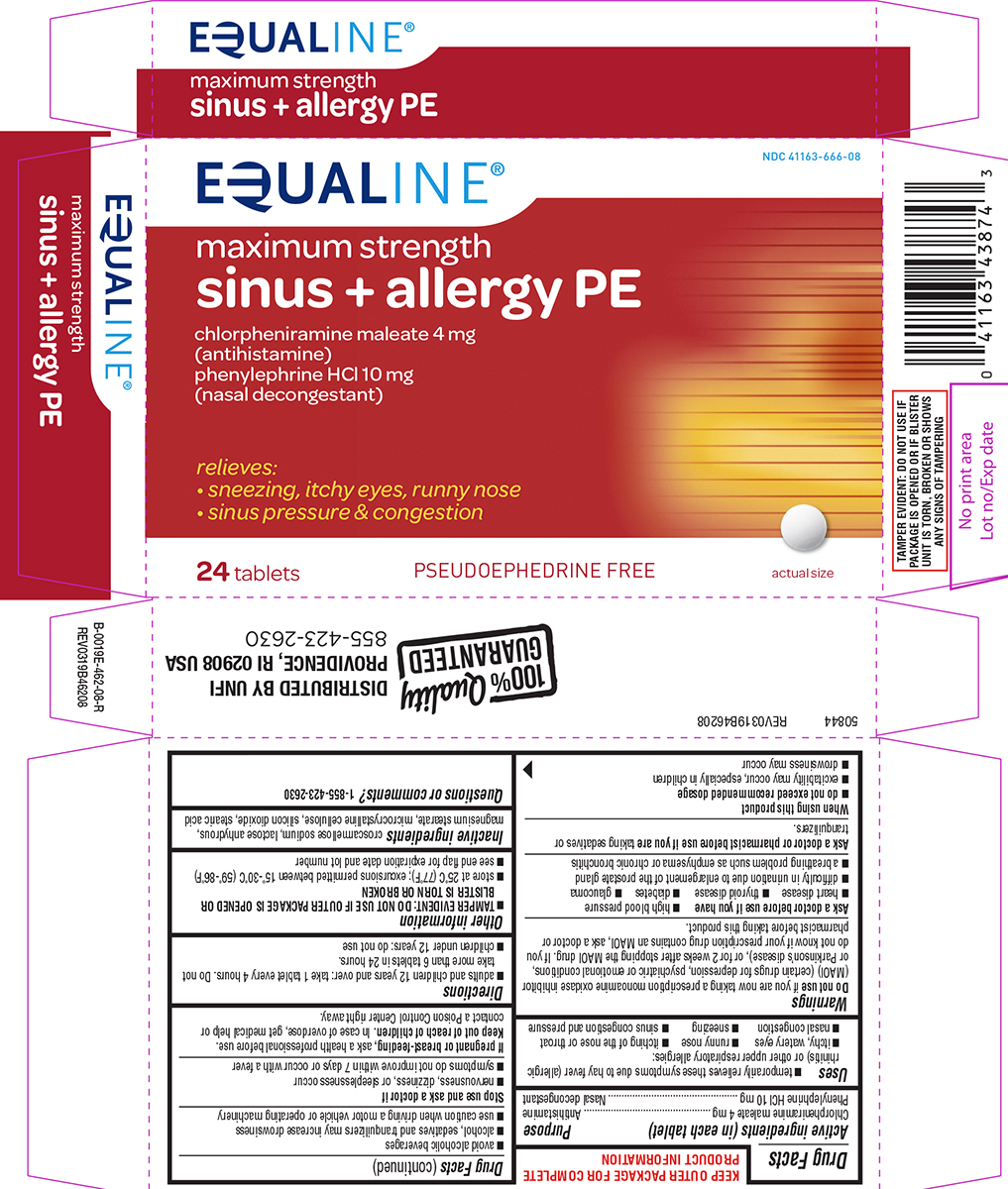 DRUG LABEL: sinus plus allergy PE
NDC: 41163-666 | Form: TABLET
Manufacturer: United Natural Foods, Inc. dba UNFI
Category: otc | Type: HUMAN OTC DRUG LABEL
Date: 20260113

ACTIVE INGREDIENTS: CHLORPHENIRAMINE MALEATE 4 mg/1 1; PHENYLEPHRINE HYDROCHLORIDE 10 mg/1 1
INACTIVE INGREDIENTS: CROSCARMELLOSE SODIUM; ANHYDROUS LACTOSE; MAGNESIUM STEARATE; MICROCRYSTALLINE CELLULOSE; SILICON DIOXIDE; STEARIC ACID

Equaline 44-462

Active ingredients (in each tablet)

Chlorpheniramine maleate 4 mg
Phenylephrine HCl 10 mg

Purpose

Antihistamine
Nasal decongestant

Uses

- temporarily relieves these symptoms due to hay fever (allergic rhinitis) or other upper respiratory allergies:
  - runny nose
  - sneezing
  - itching of the nose or throat
  - itchy, watery eyes
  - sinus congestion and pressure
  - nasal congestion

Warnings

Do not use

if you are now taking a prescription monoamine oxidase inhibitor (MAOI) (certain drugs for depression, psychiatric or emotional conditions, or Parkinson's disease), or for 2 weeks after stopping the MAOI drug. If you do not know if your prescription drug contains an MAOI, ask a doctor or pharmacist before taking this product.

Ask a doctor before use if you have

- high blood pressure
- heart disease
- thyroid disease
- diabetes
- glaucoma
- a breathing problem such as emphysema or chronic bronchitis
- difficulty in urination due to enlargement of the prostate gland

Ask a doctor or pharmacist before use if you are

taking sedatives or tranquilizers.

When using this product

- do not exceed recommended dosage
- excitability may occur, especially in children
- drowsiness may occur
- avoid alcoholic beverages
- alcohol, sedatives and tranquilizers may increase drowsiness
- use caution when driving a motor vehicle or operating machinery

Stop use and ask a doctor if

- nervousness, dizziness, or sleeplessness occur
- symptoms do not improve within 7 days or occur with a fever

If pregnant or breast-feeding,

ask a health professional before use.

Keep out of reach of children.

In case of overdose, get medical help or contact a Poison Control Center right away.

Directions

- adults and children 12 years and over: take 1 tablet every 4 hours. Do not take more than 6 tablets in 24 hours.
- children under 12 years: do not use

Other information

- TAMPER EVIDENT: DO NOT USE IF OUTER PACKAGE IS OPENED OR BLISTER IS TORN OR BROKEN
- store at 25ºC (77ºF); excursions permitted between 15º-30ºC (59º-86ºF)
- see end flap for expiration date and lot number

Inactive ingredients

croscarmellose sodium, lactose anhydrous, magnesium stearate, microcrystalline cellulose, silicon dioxide, stearic acid

Questions or comments?

1-855-423-2630

Principal Display Panel

EQUALINE®

NDC 41163-666-08

maximum strength
sinus + allergy PE

chlorpheniramine maleate 4 mg
(antihistamine)
phenylephrine HCl 10 mg
(nasal decongestant)

relieves:
• sneezing, itchy eyes, runny nose
• sinus pressure & congestion

24 tablets

PSEUDOEPHEDRINE FREE

actual size

TAMPER EVIDENT: DO NOT USE IF
PACKAGE IS OPENED OR IF BLISTER
UNIT IS TORN, BROKEN OR SHOWS
ANY SIGNS OF TAMPERING

50844 REV0319B46208

DISTRIBUTED BY UNFI
PROVIDENCE, RI 02908 USA
855-423-2630

Equaline 44-462